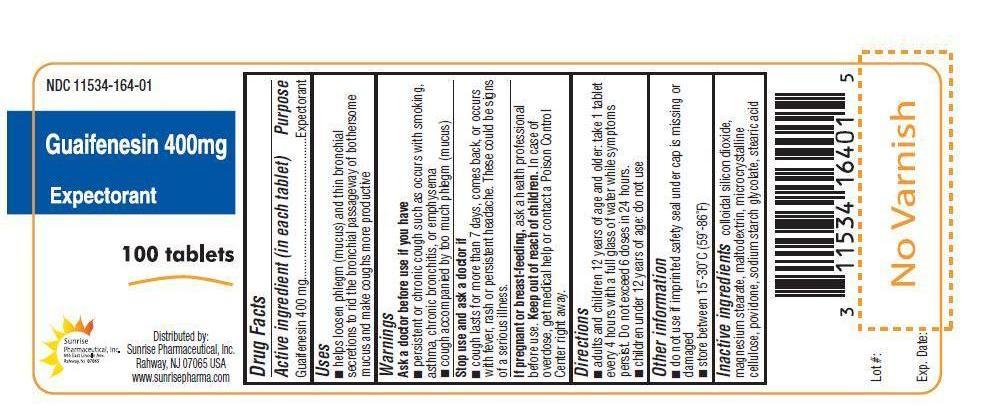 DRUG LABEL: Guiafenesin
NDC: 11534-164 | Form: TABLET
Manufacturer: Sunrise Pharmaceutical Inc
Category: otc | Type: HUMAN OTC DRUG LABEL
Date: 20130729

ACTIVE INGREDIENTS: GUAIFENESIN 400 mg/1 1
INACTIVE INGREDIENTS: SILICON DIOXIDE; MAGNESIUM STEARATE; CELLULOSE, MICROCRYSTALLINE; POVIDONE; SODIUM STARCH GLYCOLATE TYPE A POTATO; STEARIC ACID; MALTODEXTRIN

Guaifenesin 400 mg Expectorant

OTC - ACTIVE INGREDIENT

Guaifenesin 400 mg.

OTC - PURPOSE

Expectorant.

INDICATIONS AND USAGE

Helps loosen phlegm (mucus) and thin bronchial secretions to rid the bronchial passageway of bothersome mucus and make coughs more productive.

WARNINGS

Ask a doctor before use if you have

Cough that lasts or chronic such as occurs with smoking, asthma, chronic bronchitis or emphysema.

Cough accompanied by too much phlegm (mucus)

OTC - STOP USE AND ASK A DOCTOR IF

Cough lasts for more than 7 days, comes back, or occurs with fever, rash or persistent headache. These could be signs of a serious illness.

OTC – IF PREGNANT OR BREAST FEEDING

Ask a health professional before use.

OTC - KEEP OUT OF REACH OF CHILDREN

In case of overdose, get medical help or contact a Poison Control Center right away.

DIRECTIONS

Take with a glass of water

Adults and children 12 years and over | 1 tablet every 4 hour. Max 6 doses
Children 6 to under 12 years | Do not use
Children under 6 years | Do not use

OTHER INFORMATION

Store at 15(-30(C(59(-86(F)

INACTIVE INGREDIENT

Colloidal silicon dioxide, magnesium stearate, maltodextrin, microcrystalline cellulose, povidone, sodium starch glycolate, stearic acid.